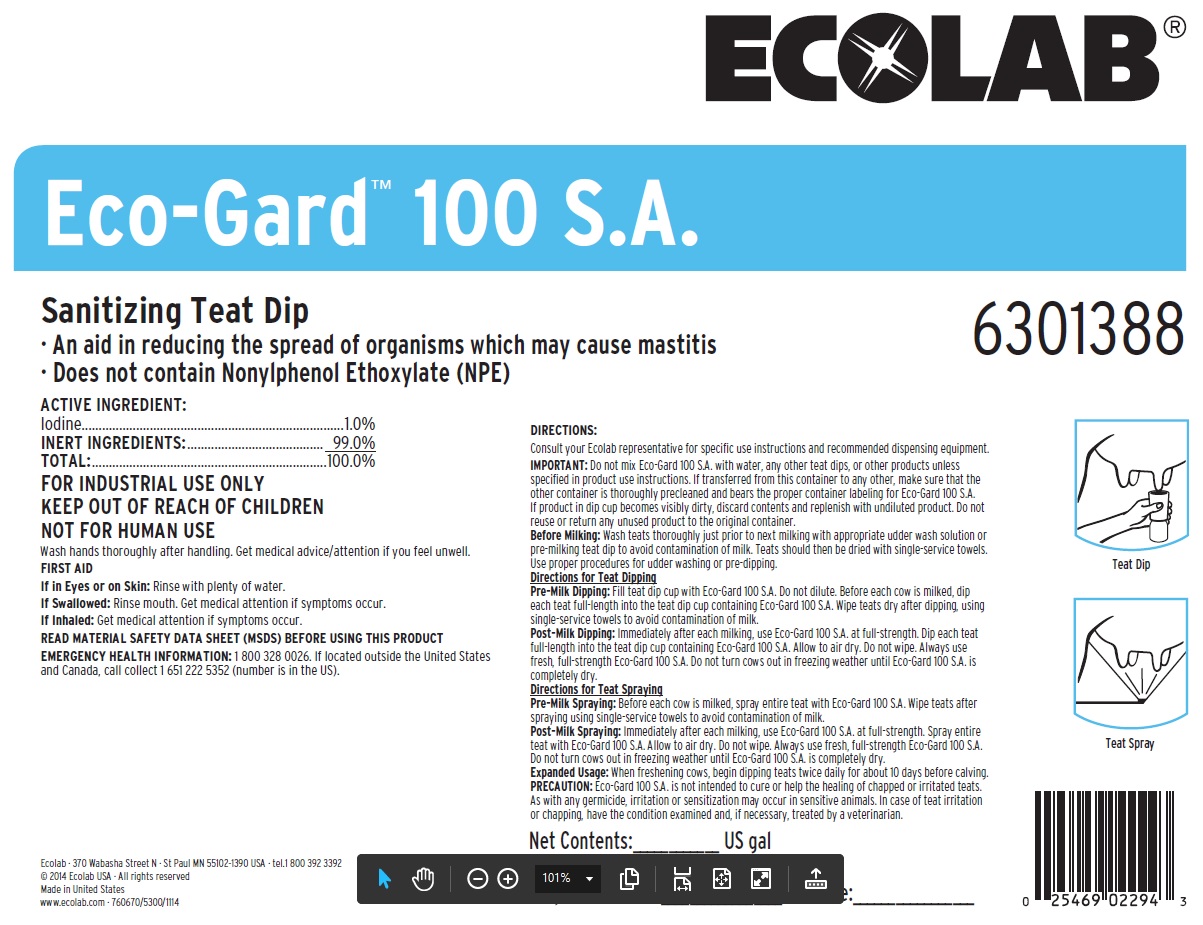 DRUG LABEL: Eco-Gard 100 S.A.
NDC: 47593-528 | Form: SOLUTION
Manufacturer: Ecolab Inc.
Category: animal | Type: OTC ANIMAL DRUG LABEL
Date: 20251027

ACTIVE INGREDIENTS: IODINE 10 mg/1 mL
INACTIVE INGREDIENTS: GLYCERIN; PROPYLENE GLYCOL; WATER

SAFE HANDLING WARNING

FOR INDUSTRIAL USE ONLY

KEEP OUT OF REACH OF CHILDREN

NOT FOR HUMAN USE

Wash hands thoroughly after handling. Get medical advice/attention if you feel unwell.

DIRECTIONS:

Consult your Ecolab representative for specific use instructions and recommended dispensing equipment.

IMPORTANT: Do not mix Eco-Gard 100 S.A. with water, any other teat dips, or other products unless specified in product use instructions. If transferred from this container to any other, make sure that the other container is thoroughly precleaned and bears the proper container labeling for Eco-Gard 100 S.A. If product in dip cup becomes visibly dirty, discard contents and replenish with undiluted product. Do not reuse or return any unused product to the original container.

Before Milking: Wash teats thoroughly just prior to next milking with appropriate udder wash solution or pre-milking teat dip to avoid contamination of milk. Teats should then be dried with single-service towels.

Use proper procedures for udder washing or pre-dipping.

Directions for Teat Dipping

Pre-Milk Dipping: Fill teat dip cup with Eco-Gard 100 S.A. Do not dilute. Before each cow is milked, dip each teat full-length into the teat dip cup containing Eco-Gard 100 S.A. Wipe teats dry after dipping, using single-service towels to avoid contamination of milk.

Post-Milk Dipping: Immediately after each milking, use Eco-Gard 100 S.A. at full-strength. Dip each teat full-length into the teat dip cup containing Eco-Gard 100 S.A. Allow to air dry. Do not wipe. Always use fresh, full-strength Eco-Gard 100 S.A. Do not turn cows out in freezing weather until Eco-Gard 100 S.A. is completely dry.

Directions for Teat Spraying

Pre-Milk Spraying: Before each cow is milked, spray entire teat with Eco-Gard 100 S.A. Wipe teats after spraying using single-service towels to avoid contamination of milk. Post-Milk Spraying: Immediately after each milking, use Eco-Gard 100 S.A. at full-strength. Spray entire teat with Eco-Gard 100 S.A. Allow to air dry. Do not wipe. Always use fresh, full-strength Eco-Gard 100 S.A.

Do not turn cows out in freezing weather until Eco-Gard 100 S.A. is completely dry.

Expanded Usage: When freshening cows, begin dipping teats twice daily for about 10 days before calving.

PRECAUTION: Eco-Gard 100 S.A. is not intended to cure or help the healing of chapped or irritated teats. As with any germicide, irritation or sensitization may occur in sensitive animals. In case of teat irritation or chapping, have the condition examined and, if necessary, treated by a veterinarian.

OTHER SAFETY INFORMATION

FIRST AID

If in Eyes or on Skin: Rinse with plenty of water.

If Swallowed: Rinse mouth. Get medical attention if symptoms occur.

If Inhaled: Get medical attention if symptoms occur.

READ MATERIAL SAFETY DATA SHEET (MSDS) BEFORE USING THIS PRODUCT

EMERGENCY HEALTH INFORMATION: 1 800 328 0026. If located outside the United States and Canada, call collect 1 651 222 5352 (number is in the US).

Representative Label and Principal Display

ECOLAB®

Eco-Gard™ 100 S.A.

Sanitizing Teat Dip

· An aid in reducing the spread of organisms which may cause mastitis
· Does not contain Nonylphenol Ethoxylate (NPE)

ACTIVE INGREDIENT:
Iodine............................................................................1.0%
INERT INGREDIENTS:................................................ 97.0%
TOTAL:......................................................................100.0%

Net Contents: US gal

Preparation Date: Lot Code:

6301388

Ecolab · 370 Wabasha Street N · St Paul MN 55102-1390 USA · tel. 800 392 3392

© 2014 Ecolab USA · All rights reserved

Made in United States

www.ecolab.com · 760670/5300/1114